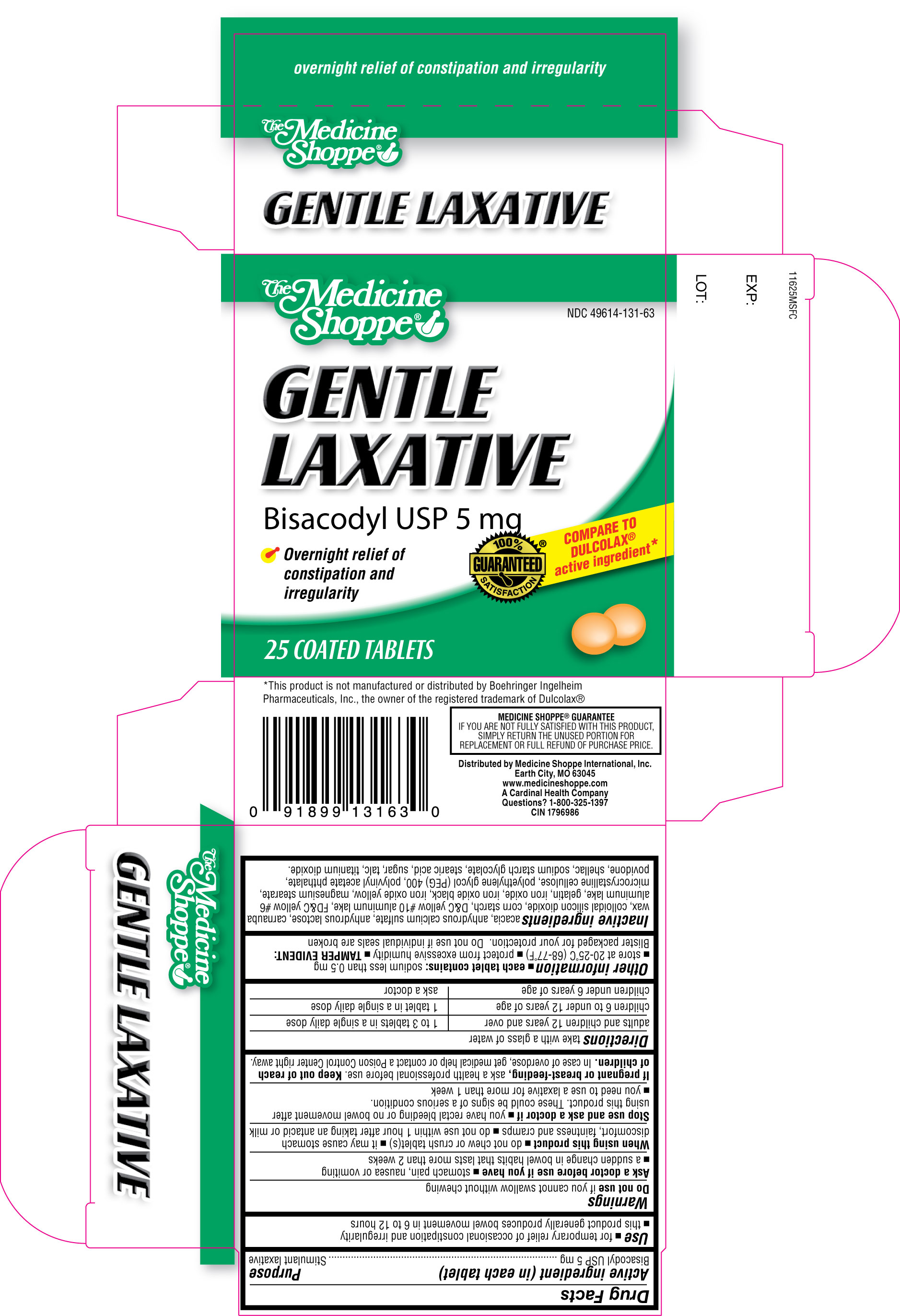 DRUG LABEL: The Medicine Shoppe Gentle Laxative
NDC: 49614-131 | Form: TABLET
Manufacturer: The Medicine Shoppe International
Category: otc | Type: HUMAN OTC DRUG LABEL
Date: 20120201

ACTIVE INGREDIENTS: BISACODYL 5 mg/1 1
INACTIVE INGREDIENTS: ACACIA; CALCIUM SULFATE ANHYDROUS; ANHYDROUS LACTOSE; CARNAUBA WAX; SILICON DIOXIDE; STARCH, CORN; D&C YELLOW NO. 10; FD&C YELLOW NO. 6; GELATIN; FERROSOFERRIC OXIDE; FERRIC OXIDE YELLOW; MAGNESIUM STEARATE; CELLULOSE, MICROCRYSTALLINE; POLYETHYLENE GLYCOL 400; POLYVINYL ACETATE PHTHALATE; POVIDONE; SHELLAC; SODIUM STARCH GLYCOLATE TYPE A POTATO; STEARIC ACID; SUCROSE; TALC; TITANIUM DIOXIDE

The Medicine Shoppe Gentle Laxative

Active ingredient(s)

Bisacodyl USP 5 mg

Purpose

Stimulant Laxative

Use(s)

- for temporary relief of occasional constipation and irregularity
- this product generally produces bowel movement in 6 to 12 hours

Warnings

Do not use

if you cannot swallow without chewing

Ask a doctor before use if you have

- stomach pain, nausea or vomiting
- a sudden change in bowel habits that lasts more than 2 weeks

When using this product

- do not chew or crush tablet(s)
- it may cause stomach discomfort, faintness or cramps
- do not use within 1 hour after taking an antacid or milk

Stop use and ask a doctor if

- you have rectal bleeding or no bowel movement after using this product. These could be signs of a serious condition.
- you need to use a laxative for more than 1 week

If pregnant or breast-feeding,

ask a health professional before use.

Keep out of reach of children.

In case of overdose, get medical help or contact a Poison Control Center right away.

Directions

take with a glass of water

adults and children 12 years and over | take 1 to 3 tablets in a single daily dose
children 6 to under 12 years of age | take 1 tablet in a single daily dose
children under 6 years of age | ask a doctor

Other information

- each tablet contains: sodium less than 0.5mg
- store at 20°-25°C (68°-77°F)
- protect from excessive humidity
- TAMPER EVIDENT: Blister packaged for your protection. Do not use if individual seals are broken

Inactive ingredients

acacia, anhydrous calcium sulfate, anhydrous lactose, carnauba wax, colloidal silicon dioxide, corn starch, D&C yellow #10 aluminum lake, FD&C yellow #6 aluminum lake, gelatin, iron oxide, iron oxide black, iron oxide yellow, magnesium stearate, microcrystalline cellulose, polyethylene glycol (PEG) 400, polyvinyl acetate phthalate, povidone, shellac, sodium starch glycolate, stearic acid, sugar, talc, titanium dioxide.

Principal Display Panel

The Medicine Shoppe

Gentle Laxative

Overnight Relief of Constipation and Irregularity

*Compare to the active ingredient of Dulcolax®

LAXATIVE

Bisacodyl USP, 5 mg

25 Coated Tablets

CIN 1796986

Distributed By:

The Medicine Shoppe International, Inc.

Earth City MO 63045

www.medicineshoppe.com

A Cardinal Health Company

Questions? 1-800-325-1397